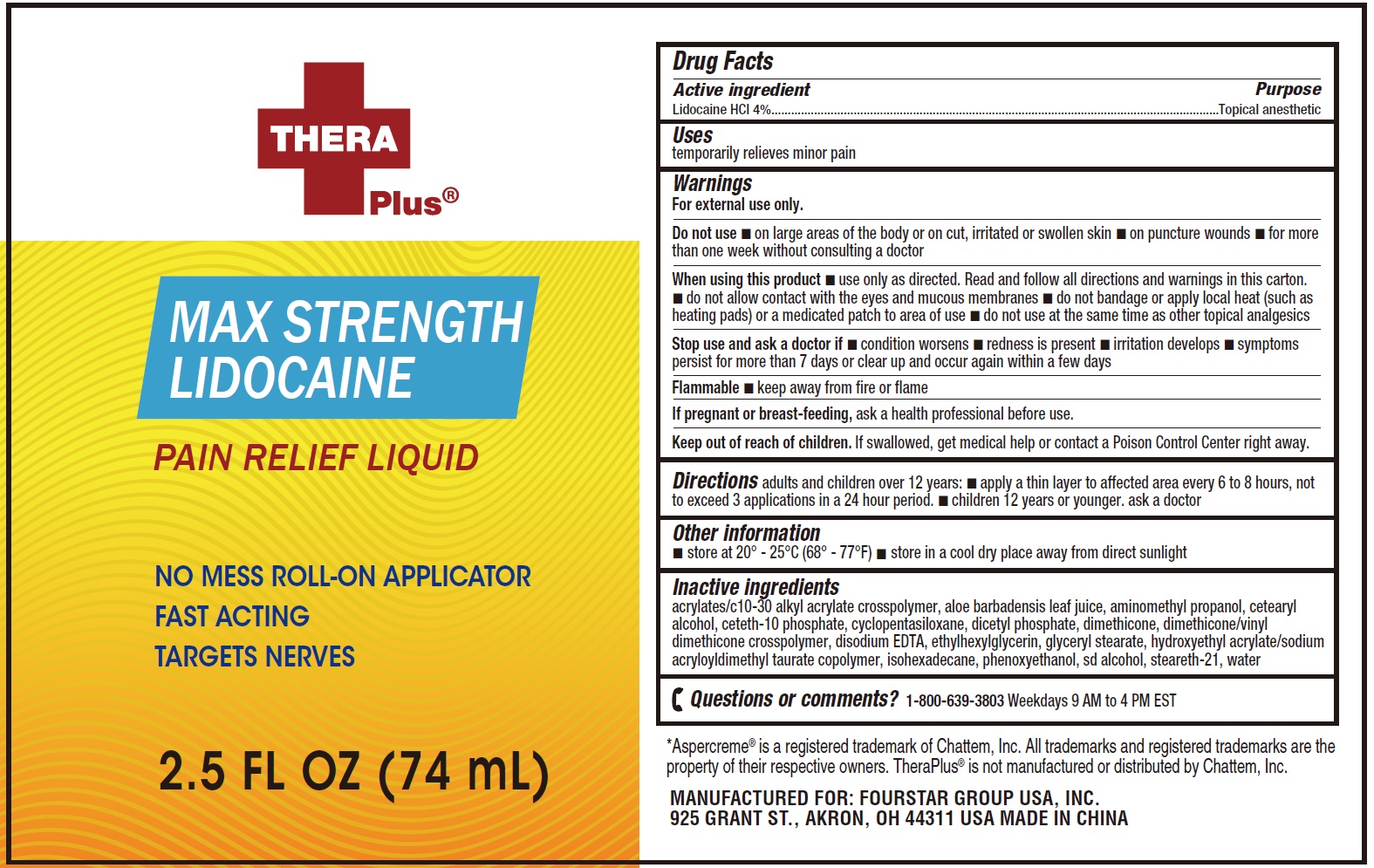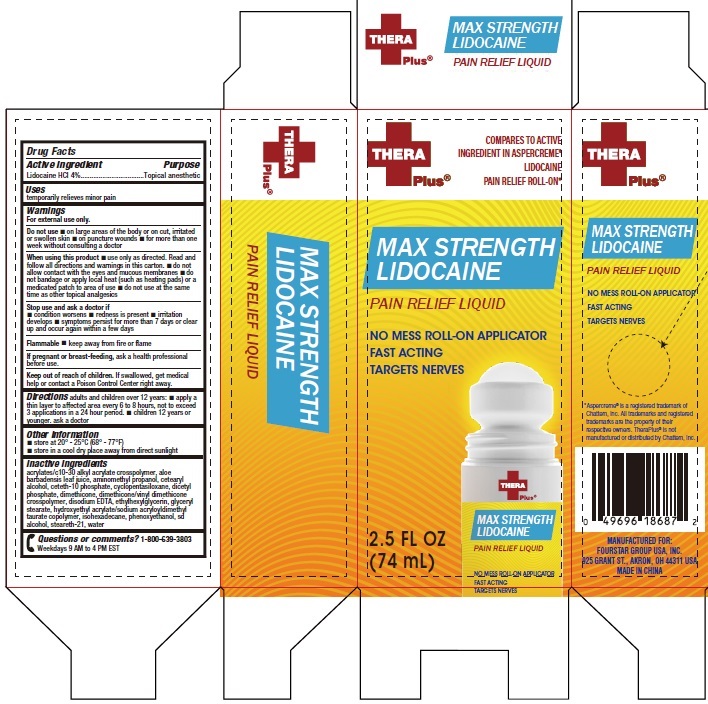 DRUG LABEL: Thera Plus Max Strength Lidocaine Pain Relief Liquid
NDC: 80684-098 | Form: LIQUID
Manufacturer: Fourstar Group USA, Inc.
Category: otc | Type: HUMAN OTC DRUG LABEL
Date: 20231130

ACTIVE INGREDIENTS: LIDOCAINE HYDROCHLORIDE 40 mg/1 mL
INACTIVE INGREDIENTS: ALOE VERA LEAF; AMINOMETHYLPROPANOL; CETOSTEARYL ALCOHOL; CETETH-10 PHOSPHATE; CYCLOMETHICONE 5; DIHEXADECYL PHOSPHATE; DIMETHICONE; EDETATE DISODIUM ANHYDROUS; ETHYLHEXYLGLYCERIN; GLYCERYL MONOSTEARATE; ISOHEXADECANE; PHENOXYETHANOL; STEARETH-21; WATER

Thera Plus Max Strength Lidocaine Pain Relief Liquid

Active ingredient

Lidocaine HCI 4%

Purpose

Topical analgesic

Uses

temporarily relieves minor pain

Warnings

For external use only.

Flammable •keep away from fire or flame

Do not use

• on large areas of the body or on cut, irritated or swollen skin • on puncture wounds • for more than one week without consulting a doctor

When using this product

• use only as directed. Read and follow all directions and warnings in this carton. • do not allow contact with the eyes and mucous membranes • do not bandage or apply local heat (such as heating pads) or a medicated patch to area of use • do not use at the same time as other topical analgesics

Stop use and ask a doctor if

• condition worsens • redness is present • irritation develops • symptoms persist for more than 7 days or clear up and occur again within a few days

If pregnant or breast-feeding,

ask a health professional before use.

Keep out of reach of children.

If swallowed, get medical help or contact a Poison Control Center right away.

Directions

adults and children over 12 years: • apply a thin layer to affected area every 6 to 8 hours, not to exceed 3 applications in a 24 hour period. • children 12 years or younger. ask a doctor

Other information

- store at 20° - 25°C (68° - 77°F)
- store in a cool dry place away from direct sunlight

Inactive ingredients

acrylates/c10-30 alkyl acrylate crosspolymer, aloe barbadensis leaf juice, aminomethyl propanol, cetearyl alcohol, ceteth-10 phosphate, cyclopentasiloxane, dicetyl phosphate, dimethicone, dimethicone/vinyl dimethicone crosspolymer, disodium EDTA, ethylhexylglycerin, glyceryl stearate, hydroxyethyl acrylate/sodium acryloyldimethyl taurate copolymer, isohexadecane, phenoxyethanol, sd alcohol, steareth-21, water

Questions or comments?

1-800-639-3803 Weekdays 9 AM to 4 PM EST